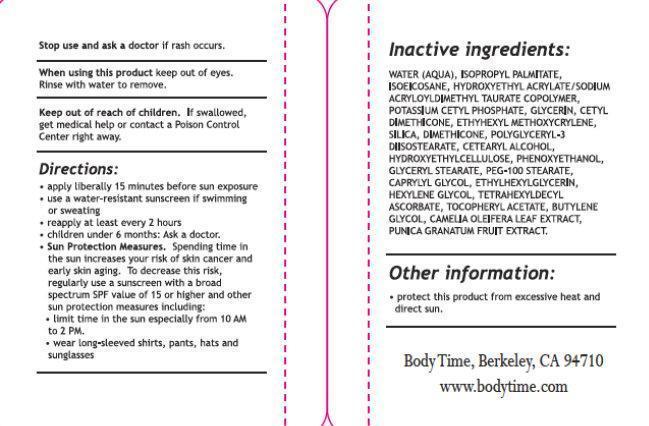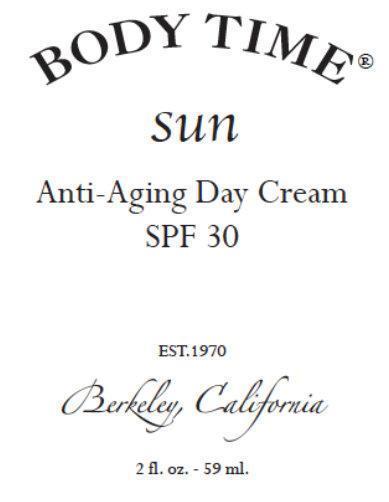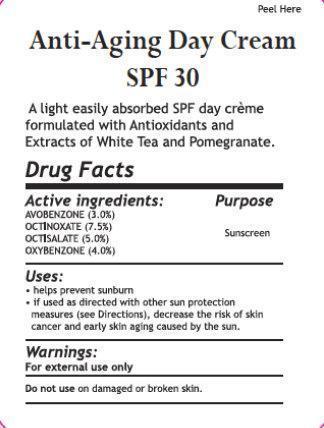 DRUG LABEL: BODY TIME Anti-Aging Day Cream SPF 30
NDC: 61979-001 | Form: CREAM
Manufacturer: Bela Vida Holdings, LLC dba Body Time
Category: otc | Type: HUMAN OTC DRUG LABEL
Date: 20140721

ACTIVE INGREDIENTS: OCTINOXATE 75 mg/1 mL; AVOBENZONE 30 mg/1 mL; OCTISALATE 50 mg/1 mL; OXYBENZONE 40 mg/1 mL
INACTIVE INGREDIENTS: WATER; ISOPROPYL PALMITATE; ISOEICOSANE; HYDROXYETHYL ACRYLATE/SODIUM ACRYLOYLDIMETHYL TAURATE COPOLYMER (45000 MPA.S AT 1%); POTASSIUM CETYL PHOSPHATE; GLYCERIN; CETYL DIMETHICONE 25; ETHYLHEXYL METHOXYCRYLENE; SILICA DIMETHYL SILYLATE; DIMETHICONE; POLYGLYCERYL-3 DIISOSTEARATE; CETOSTEARYL ALCOHOL; HYDROXYMETHYL CELLULOSE; PHENOXYETHANOL; GLYCERYL MONOSTEARATE; PEG-100 STEARATE; CAPRYLYL GLYCOL; ETHYLHEXYLGLYCERIN; HEXYLENE GLYCOL; TETRAHEXYLDECYL ASCORBATE; .ALPHA.-TOCOPHEROL ACETATE; BUTYLENE GLYCOL; POMEGRANATE

BODY TIME Anti-Aging Day Cream SPF 30

Active Ingredients

Avobenzone 3.0%

Octinoxate 7.5%

Octisalate 5.0%

Oxybenzone 4.0%

Purpose

Sunscreen

Use

- Helps prevent sunburn.
- If used as directed with other sun protection measures (see Directions), decreases the risk of skin cancer and early skin aging caused by the sun.

Warnings

For external use only

Do not use on damaged or broken skin

When using this product keep out of eyes. Rinse with water to remove.

Stop use and ask a doctor if rash occurs

Keep out of reach of children.

If swallowed, get medical help or contact a Poison Control Center right away.

Directions

- apply liberally 15 minutes before sun exposure
- Reapply at least every 2 hours
- Use a water resistant sunscreen if swimming or sweating
- Children under 6 months of age: Ask a doctor
- Sun Protection Measures.
  Spending time in the sun increases your risk of skin cancer and early skin aging. To
  decrease the risk, regularly uses a sunscreen with a Broad Spectrum SPF value of 15 or higher and other sun protection measures including:
- Limit time in the sun, especially from 10 a.m. to 2 p.m.
- Wear long- sleeved shirts, pants, hats and sunglasses

Other Information

Protect the product in this container from excessive heat and direct sun

Inactive Ingredients

WATER (AQUA), ISOPROPYL PALMITATE, ISOEICOSANE, HYDROXYETHYLACRYLATE/SOOIUM ACRYLOYLDIMETHYL TAURATE COPOLYMER, POTASSIUM CETYL PHOSPHATE, GLYCERIN, CETYL DIMETHICONE, ETHYHEXYL METHOXYCRYLENE, SILICA, DIMETHICOHE, POLYGLYCERYL-3 DIISOSTEARATE, CETEARYL ALCOHOL,HYDROXYMETHYL CELLULOSE, PHENOXYETHANOL, GLYCERYL STEARATE, PEG-1OO STEARATE, CAPRYLYL GLYCOL, ETHYLHEXYLGLYCERIN,HEXYLENE GLYCOL, TETRAHEXYLDECYL ASCORBATE, TOCOPHERYl ACETATE, BUTYLENE GLYCOL, CAMELIA OLEIFERA LEAF EXTRACT, PUNICA GRANATUM FRUIT EXTRACT.

Body Time, Berkeley, CA 94710

www.bodytime.com

BODY TIME Anti-Aging Day Cream SPF 30, 2 fl. 0Z (59 ml) (61979-001-59)

BODY TIME

sun

Anti-Aging Day Cream

SPF 30

EST.1970

Berkeley, California

2 fl. 0Z . • 59 ml.

Anti-Aging Day Cream

SPF 30

A light easily absorbed SPF day creme formulated with Antioxidants and Extracts of White Tea and Pomegranate.